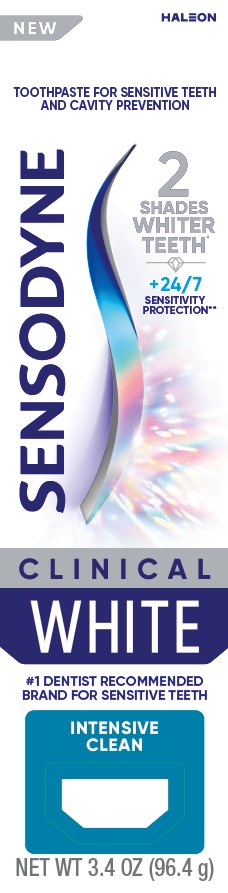 DRUG LABEL: Sensodyne
NDC: 0135-5468 | Form: PASTE
Manufacturer: Haleon US Holdings LLC
Category: otc | Type: HUMAN OTC DRUG LABEL
Date: 20241231

ACTIVE INGREDIENTS: POTASSIUM NITRATE 50 mg/1 g; SODIUM FLUORIDE 1.1 mg/1 g
INACTIVE INGREDIENTS: WATER; SORBITOL; HYDRATED SILICA; GLYCERIN; SODIUM TRIPOLYPHOSPHATE ANHYDROUS; PEG-8 MONOSTEARATE; SODIUM LAURYL SULFATE; ALUMINUM OXIDE; TITANIUM DIOXIDE; XANTHAN GUM; COCAMIDOPROPYL BETAINE; SODIUM HYDROXIDE; CARRAGEENAN; SACCHARIN SODIUM

Drug Facts

Active ingredients

Potassium nitrate 5%

Sodium fluoride 0.25% (0.15% w/v fluoride ion)

Purposes

Antihypersensitivity

Anticavity

Uses

- builds increasing protection against painful sensitivity of the teeth to cold, heat, acids, sweets, or contact.
- aids in the prevention of dental cavities

Warnings

Stop use and ask a dentist if

- the problem persists or worsens. Sensitive teeth may indicate a serious problem that may need prompt care by a dentist.
- pain/sensitivity still persists after 4 weeks of use.

Keep out of reach of children.

If more than used for brushing is accidentally swallowed, get medical help or contact a Poison Control Center right away.

Directions

- adults and children 12 years of age and older:
  - apply at least a 1-inch strip of the product onto a soft bristle toothbrush.
  - brush teeth thorough for at least 1 minute twice a day (morning and evening), and not more than 3 times a day, or as recommended by a dentist or doctor. Make sure to brush all sensitive areas of the teeth. Minimize swallowing. Spit out after brushing.
- children under 12 years of age: Consult a dentist or doctor.

Other information

- do not store above 25°C (77°F)

Inactive ingredients

water, sorbitol, hydrated silica, glycerin, pentasodium triphosphate, PEG-8, sodium lauryl sulfate, flavor, alumina, titanium dioxide, xanthan gum, cocamidopropyl betain, sodium hydroxide, carrageenan, sodium saccharin

Questions or comments?

1-866-844-2797

Generic Section

ALWAYS FOLLOW THE LABEL

SENSODYNE

WHITE

CLINICALLY PROVEN WHITENING DESIGNED FOR SENSITIVE TEETH

WHITENING

Clinically proven whitening ingredients remove stains, polish teeth and help prevent future stains

SENSITIVITY PROTECTION

Clinically proven ingredients to protect against sensitivity and strengthen enamel

7X BETTER CLEANING^

Through stain removal

ENAMEL SAFE

* As shown in an 8 week study.

** With twice daily brushing.

^ After 8 weeks twice daily brushing as compared to a non-whitening toothpaste.

Principal Display Panel

TOOTHPASTE FOR SENSITIVE TEETH AND CAVITY PREVENTION

SENSODYNE

2 SHADES WHITER TEETH*

+ 24/7 SENSITIVITY PROTECTION**

CLINICAL WHITE

#1 DENTIST RECOMMENDED BRAND FOR SENSITIVE TEETH

INTENSIVE CLEAN

NET WT 3.4 OZ (96.4 g)